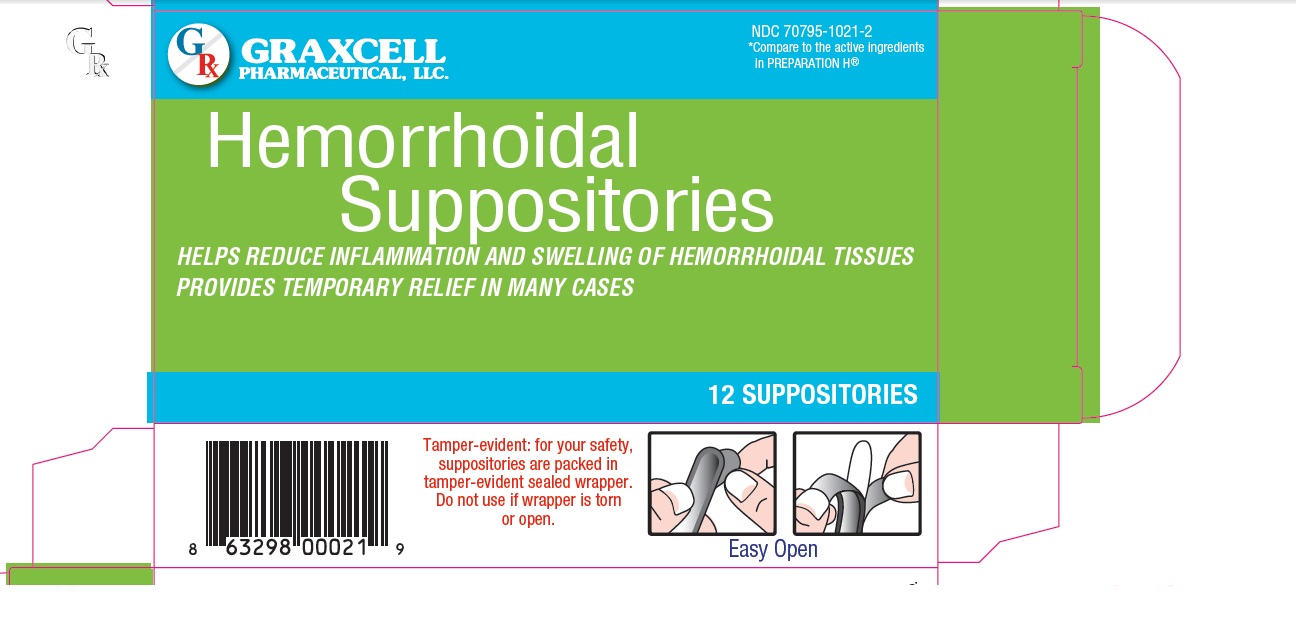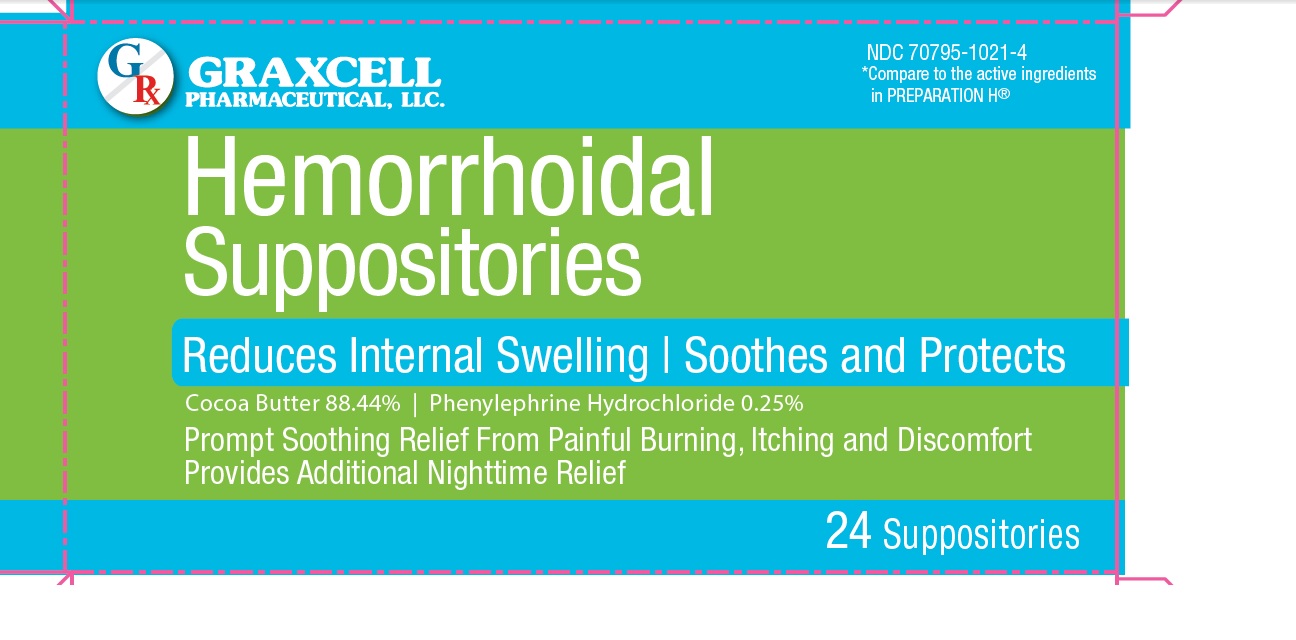 DRUG LABEL: Hemorrhoidal
NDC: 70795-1021 | Form: SUPPOSITORY
Manufacturer: GRAXCELL PHARMACEUTICAL, LLC
Category: otc | Type: HUMAN OTC DRUG LABEL
Date: 20251225

ACTIVE INGREDIENTS: COCOA BUTTER 1768.8 mg/1 1; PHENYLEPHRINE HYDROCHLORIDE 5 mg/1 1
INACTIVE INGREDIENTS: METHYLPARABEN; PROPYLPARABEN; STARCH, CORN

GRAXCELL PHARMACEUTICAL - HEMORRHOIDAL SUPPOSITORIES, 70795-1021

Active Ingredients (per suppository)

Cocoa butter 88.44 %

Phenylephrine hydrochloride 0.25 %

Purpose

Protectant

Vasoconstructor

Uses

- temporarily shrinks hemorrhoidal tissues
- gives temporary relief to the itching, burning and discomfort associated with hemorrhoids
- aids in protecting irritated anorectal areas

Warnings

For rectal use only

Ask a doctor or pharmacist before use if you are

presently taking a prescription drug for high blood pressure or depression

Ask a doctor before use if you have

- heart disease
- thyroid disease
- high blood pressure
- diabetes
- difficulty in urination due to enlargement of the prostate gland

When using this product

- do not exceed the recommended daily dosage unless directed by a doctor
- in case of bleeding or if condition worsens or does not improve within 7 days, consult a doctor promptly

If pregnant or breast-feeding

ask a health professional before use.

Keep out of reach of children

If swallowed, get medical help or contact a Poison Control Center right away.

Directions Adults

- detach one suppository from the strip. Remove the wrapper before inserting into the rectum.
- insert one suppository into the rectum up to 4 times daily, especially at night, in the morning or after each bowel movement. Children under 12 years of age: consult doctor

Other Information

Store at room temperature or in a cool place but not over 80° F

Inactive ingredients

methylparaben, propylparaben, starch